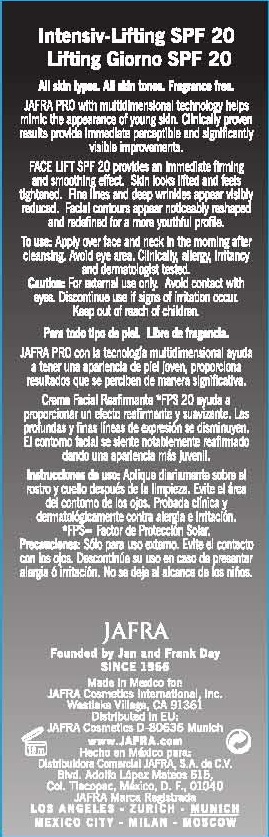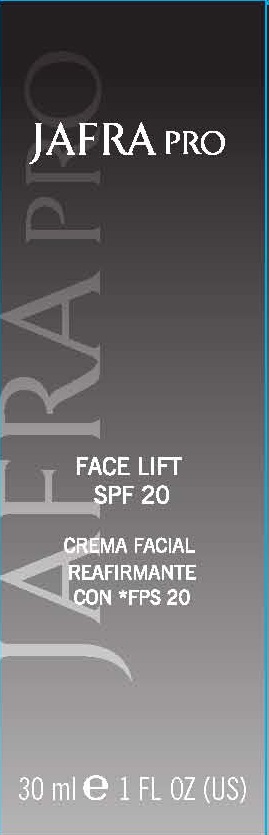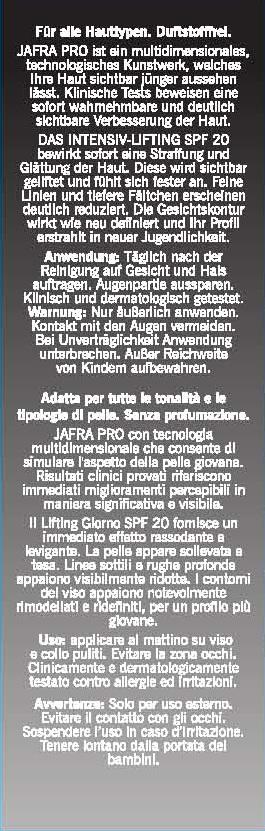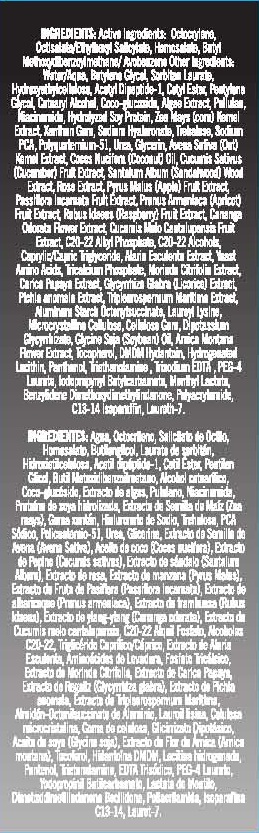 DRUG LABEL: JAFRA PRO FACE LIFT
NDC: 68828-049 | Form: LOTION
Manufacturer: JAFRA COSMETICS INTERNATIONAL
Category: otc | Type: HUMAN OTC DRUG LABEL
Date: 20120514

ACTIVE INGREDIENTS: OCTOCRYLENE 7 g/100 mL; OCTISALATE 5 g/100 mL; HOMOSALATE 5 g/100 mL; AVOBENZONE 3 g/100 mL
INACTIVE INGREDIENTS: BUTYLENE GLYCOL; SORBITAN MONOLAURATE; HYDROXYETHYL CELLULOSE (100 MPA.S AT 2%); N-ACETYL DIPEPTIDE-1; CETYL ESTERS WAX; CETOSTEARYL ALCOHOL; COCO GLUCOSIDE; MACROCYSTIS PYRIFERA; PULLULAN; NIACINAMIDE; SOY PROTEIN; CORN; XANTHAN GUM; HYALURONATE SODIUM; TREHALOSE; SODIUM PYRROLIDONE CARBOXYLATE; POLIDRONIUM CHLORIDE; UREA; GLYCERIN; OAT; COCONUT OIL; CUCUMBER JUICE; SANDALWOOD; ROSA DAMASCENA FLOWER OIL; APPLE JUICE; PASSIFLORA INCARNATA FRUIT; APRICOT JUICE; RASPBERRY JUICE; CANANGA ODORATA FLOWER; MUSKMELON; C20-22 ALKYL PHOSPHATE; C20-22 ALCOHOLS; MEDIUM-CHAIN TRIGLYCERIDES; ALARIA ESCULENTA; YEAST; TRICALCIUM PHOSPHATE; MORINDA CITRIFOLIA LEAF; PAPAYA JUICE; GLYCYRRHIZA GLABRA; PICHIA JADINII; BETA VULGARIS POLLEN; ALUMINUM STARCH OCTENYLSUCCINATE; LAUROYL LYSINE; CELLULOSE, MICROCRYSTALLINE; CARBOXYMETHYLCELLULOSE SODIUM; GLYCYRRHIZINATE DIPOTASSIUM; SOYBEAN OIL; ARNICA MONTANA FLOWER; TOCOPHEROL; DMDM HYDANTOIN; HYDROGENATED SOYBEAN LECITHIN; PANTHENOL; TROLAMINE; EDETATE TRISODIUM; PEG-4 LAURATE; IODOPROPYNYL BUTYLCARBAMATE; MENTHYL LACTATE, (-)-; BENZYLIDENE DIMETHOXYDIMETHYLINDANONE; POLYACRYLAMIDE (1500 MW); C13-14 ISOPARAFFIN; LAURETH-7; WATER

FACE LIFT SPF 20

ACTIVE INGREDIENTS:

- OCTOCRYLENE
- OCTISALATE/ETHYLHEXYL SALICYLATE
- HOMOSALATE
- BUTYL METHOXYDIBENZOYLMETHANE/AVOBENZONE

PURPOSE: SUNSCREEN

INACTIVE INGREDIENT

INGREDIENTS: WATER/AQUA, BUTYLENE GLYCOL, SORBITAN LAURATE, HYDROXYETHYLCELLULOSE, ACETYL DIPEPTIDE-1, CETYL ESTER, PENTYLENE GLYCOL, CETEARYL ALCOHOL, COCO-GLUCOSIDE, ALGAE EXTRACT, PULLULAN, NIACINAMIDE, HYDROLYZED SOY PROTEIN, ZEA MAYS (CORN) KERNEL EXTRACT, XANTHAN GUM, SODIUM HYALURONATE, TREHALOSE, SODIUM PCA, POLYQUATERNIUM-51, UREA, GLYCERIN, AVENA SATIVA (OAT) KERNEL EXTRACT, COCOS NUCIFERA (COCONUT) OIL, CUCUMIS SATIVUS (CUCUMBER) FRUIT EXTRACT, SANTALUM ALBUM (SANDALWOOD) WOOD EXTRACT, ROSE EXTRACT, PYRUS MALUS (APPLE) FRUIT EXTRACT, PASSIFLORA INCARNATA FRUIT EXTRACT, PRUNUS ARMENIACA (APRICOT) FRUIT EXTRACT, RUBUS IDAEUS (RASPBERRY) FRUIT EXTRACT, CANANGA ODORATA FLOWER EXTRACT, CUCUMIS MELO CANTALUPENSIS FRUIT EXTRACT, C20-22 ALKYL PHOSPHATE, C20-22 ALCOHOLS, CAPRYLIC/CAPRIC TRIGLYCERIDES, ALARIA ESCULENTA EXTRACT, YEAST AMINO ACIDS, TRICALCIUM PHOSPHATE, MORINDA CITRIFOLIA EXTRACT, CARICA PAPAYA EXTRACT, GLYCYRRHIZA GLABRA (LICORICE) EXTRACT, PICHIA ANOMALA EXTRACT, TRIPLEUROSPERMUM MARITIMA EXTRACT, ALUMINUM STARCH OCTENYLSUCCINATE, LAUROYL LYSINE, MICROCRYSTALLINE CELLULOSE, CELLULOSE GUM, DIPOTASSIUM GLYCYRRHIZATE, GLYCINE SOYA (SOYBEAN) OIL, ARNICA MONTANA FLOWER EXTRACT, TOCOPHEROL, DMDM HYDANTOIN, HYDROGENATED LECITHIN, PANTHENOL, TRIETHANOLAMINE, TRISODIUM EDTA, PEG-4 LAURATE, IODOPROPYNYL BUTYLCARBAMATE, MENTHYL LACTATE, BENZYLIDENE DIMETHOXYDIMETHYLINDANONE, POLYACRYLAMIDE, C13-14 ISOPARAFFIN, LAURETH-7.

INDICATIONS AND USAGE

ALL SKIN TYPES. ALL SKIN TONES. FRAGRANCE FREE.

DOSAGE AND ADMINISTRATION

TO USE: APPLY OVER FACE AND NECT IN THE MORNING AFTER CLEANSING.

DISCONTINUE USE IF SIGNS OF IRRITATION OCCUR.

KEEP OUT OF REACH OF CHILDREN.

PACKAGE LABEL

JAFRA PRO

FACE LIFT

SPF 20

30 ML / 1 FL OZ (US)

WARNINGS

CAUTION: FOR EXTERNAL USE ONLY. AVOID CONTACT WITH EYES.